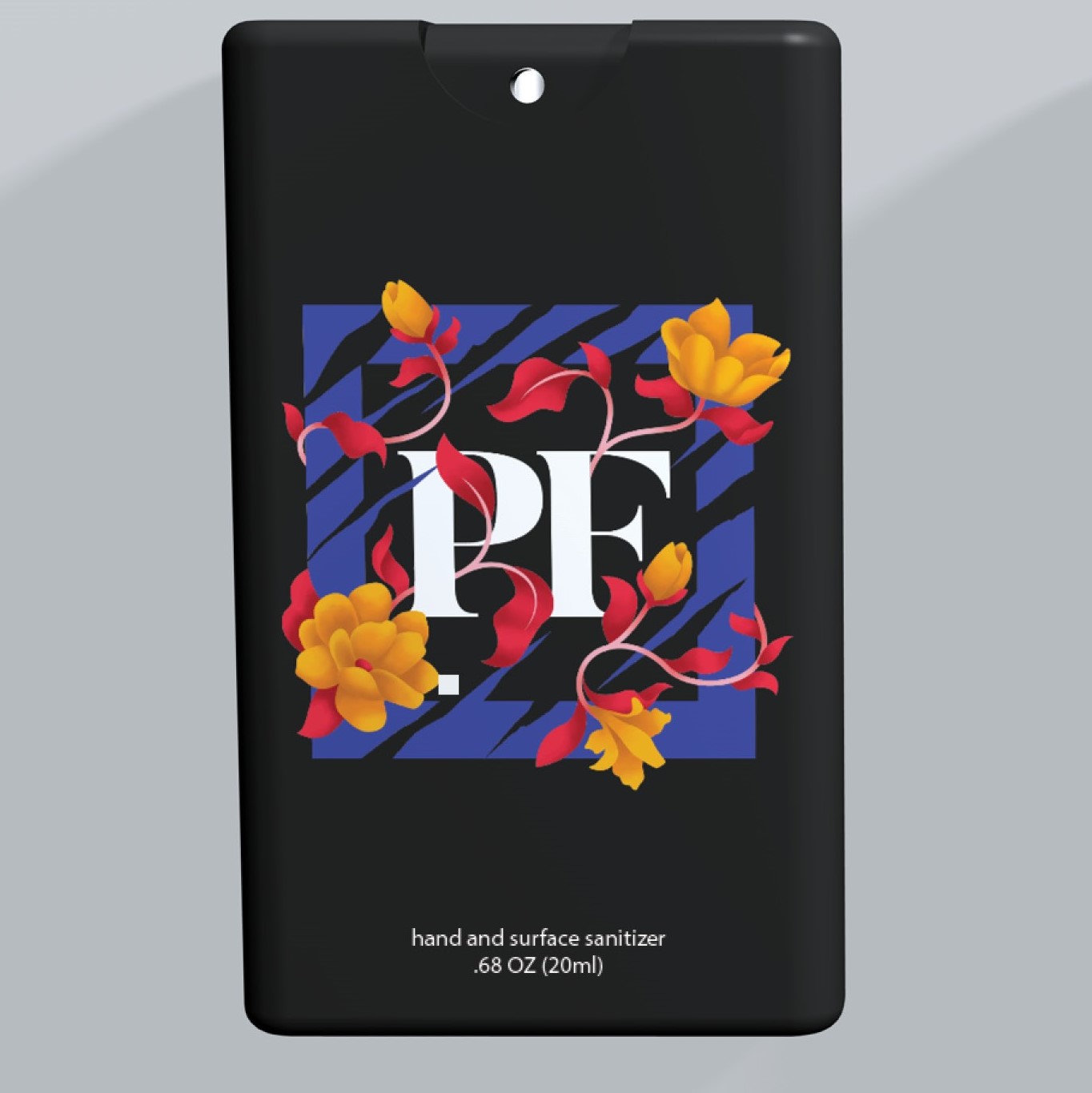 DRUG LABEL: OHHY Secure
NDC: 79372-007 | Form: LIQUID
Manufacturer: OHHY Media
Category: otc | Type: HUMAN OTC DRUG LABEL
Date: 20210329

ACTIVE INGREDIENTS: ALCOHOL 14 mL/20 mL
INACTIVE INGREDIENTS: GLYCERIN; WATER

Active Ingredient(s)

Alcohol 70% v/v.

Purpose

Antiseptic

Use

Hand Sanitizer to help reduce bacteria that potentially can cause disease. For use when soap and water are not available.

Warnings

For external use only. Flammable. Keep away from heat or flame

Do not use

in children less than 2 months of age

on open skin wounds

When using this product keep out of eyes, ears, and mouth. In case of contact with eyes, rinse eyes thoroughly with water.

Stop use and ask a doctor if irritation or rash occurs. These may be signs of a serious condition.

Keep out of reach of children. If swallowed, get medical help or contact a Poison Control Center right away.

Stop use and ask a doctor if irritation or rash occurs. These may be signs of a serious condition.

Keep out of reach of children. If swallowed, get medical help or contact a poison Control Center right away.

Directions

Place enough product on hands to cover all surfaces. Rub hands together until dry.

Supervise children under 6 years of age when using this product to avoid swallowing.

other information

Store between 15-30C (59-86F)

Avoid freezing and excessive heat above 40C (104F)

Inactive ingredients

glycerin, purified water USP

STATEMENT OF IDENTITY

OHHY Media- 125 Wes Walker Memorial Dr. -Ball Ground, GA 30107

oh-hy.com

Questions? Call 800-255-0262

Manufactured by Central Solutions Inc For OHHY Media

Distributed by OHHY Media SANI14104REV0715

POSTMARKETING EXPERIENCE

To order additional Sanitizer, place your order at www.ohhymedia.com/sanitizer For further inquiries, contact us through our website at: www.ohhymedia.com

PACKAGE LABEL

hand and surface sanitizer

.68 OZ (20ML)